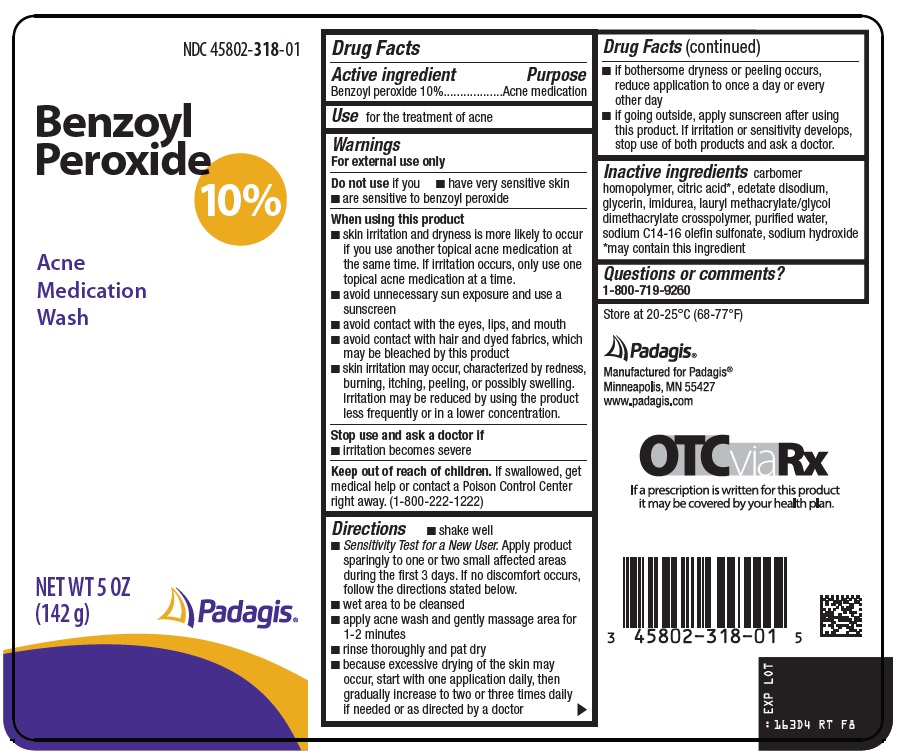 DRUG LABEL: benzoyl peroxide
NDC: 45802-318 | Form: SUSPENSION
Manufacturer: Padagis Israel Pharmaceuticals Ltd
Category: otc | Type: HUMAN OTC DRUG LABEL
Date: 20250212

ACTIVE INGREDIENTS: BENZOYL PEROXIDE 10 g/100 g
INACTIVE INGREDIENTS: CITRIC ACID MONOHYDRATE; EDETATE DISODIUM; GLYCERIN; IMIDUREA; LAURYL METHACRYLATE/GLYCOL DIMETHACRYLATE CROSSPOLYMER; WATER; SODIUM C14-16 OLEFIN SULFONATE; SODIUM HYDROXIDE

Benzoyl Peroxide 10% Drug Facts

Active ingredient

Benzoyl peroxide 10%

Purpose

Acne medication

Use

for the treatment of acne

Warnings

For external use only

Do not use

if you

- have very sensitive skin
- are sensitive to benzoyl peroxide

When using this product

- skin irritation and dryness is more likely to occur if you use another topical acne medication at the same time. If irritation occurs, only use one topical acne medication at a time.
- avoid unnecessary sun exposure and use a sunscreen
- avoid contact with the eyes, lips, and mouth
- avoid contact with hair and dyed fabrics, which may be bleached by this product
- skin irritation may occur, characterized by redness, burning, itching, peeling, or possibly swelling. Irritation may be reduced by using the product less frequently or in a lower concentration.

Stop use and ask a doctor if

- irritation becomes severe

Keep out of reach of children.

If swallowed, get medical help or contact a Poison Control Center right away. (1-800-222-1222)

Directions

- shake well
- Sensitivity Test for a New User. Apply product sparingly to one or two small affected areas during the first 3 days. If no discomfort occurs, follow the directions stated below.
- wet area to be cleansed
- apply acne wash and gently massage area for 1-2 minutes
- rinse thoroughly and pat dry
- because excessive drying of the skin may occur, start with one application daily, then gradually increase to two or three times daily if needed or as directed by a doctor
- if bothersome dryness or peeling occurs, reduce application to once a day or every other day
- if going outside, apply sunscreen after using this product. If irritation or sensitivity develops, stop use of both products and ask a doctor.

Inactive ingredients

carbomer homopolymer, citric acid*, edetate disodium, glycerin, imidurea, lauryl methacrylate/glycol dimethacrylate crosspolymer, purified water, sodium C14-16 olefin sulfonate, sodium hydroxide

*may contain this ingredient

Questions or comments?

1-800-719-9260

Package/Label Principal Display Panel

Benzoyl Peroxide 10%

Acne Medication Wash

NET WT 5 OZ (142 g)

Padagis®